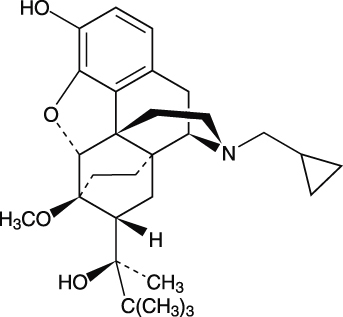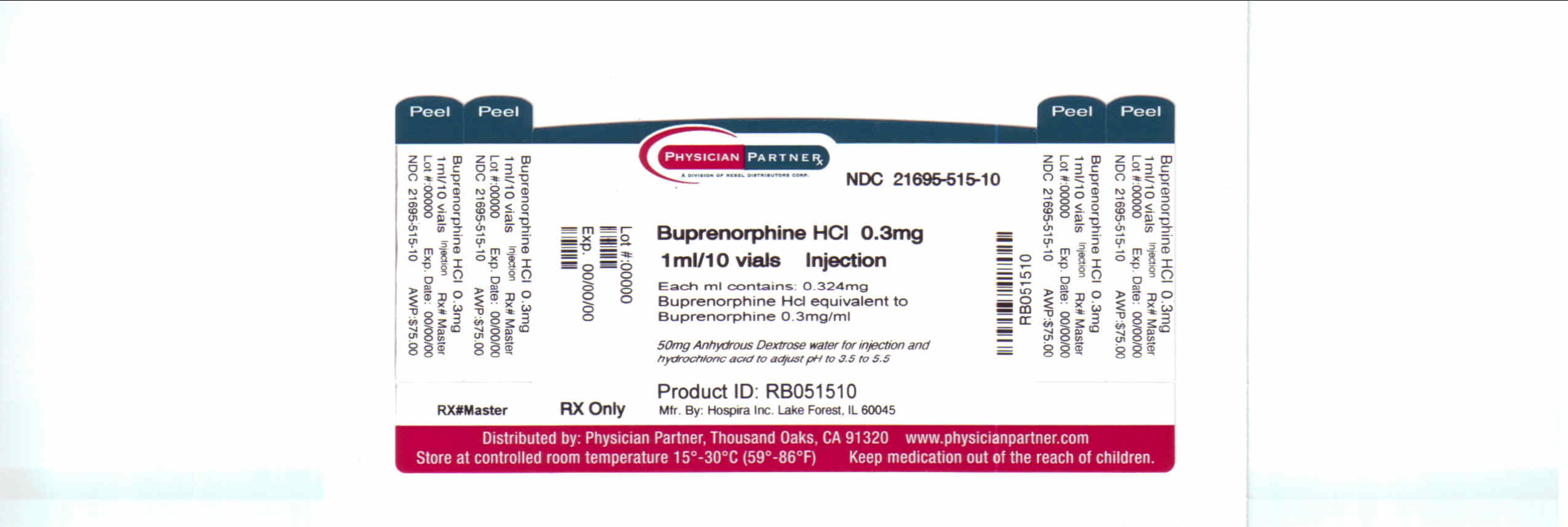 DRUG LABEL: Buprenorphine Hydrochloride
NDC: 21695-515 | Form: INJECTION, SOLUTION
Manufacturer: Rebel Distributors Corp
Category: prescription | Type: HUMAN PRESCRIPTION DRUG LABEL
Date: 20101210
DEA Schedule: CIII

ACTIVE INGREDIENTS: BUPRENORPHINE HYDROCHLORIDE 0.3 mg/1 mL
INACTIVE INGREDIENTS: ANHYDROUS DEXTROSE 50 mg/1 mL; WATER; HYDROCHLORIC ACID

Buprenorphine
Hydrochloride
Injection

CIII

Rx only

DESCRIPTION

Buprenorphine hydrochloride is a narcotic under the Controlled Substances Act due to its chemical derivation from thebaine. Chemically, it is 17-(cyclopropylmethyl)-α-(1,1-dimethylethyl)-4,5-epoxy-18,19-dihydro-3-hydroxy-6-methoxy-α-methyl-6,14-ethenomorphinan-7-methanol, hydrochloride [5α, 7α(S)]. Buprenorphine hydrochloride is a white powder, weakly acidic and with limited solubility in water. Buprenorphine hydrochloride injection is a clear, sterile, injectable agonist-antagonist analgesic intended for intravenous or intramuscular administration. Each mL of buprenorphine hydrochloride injection contains 0.324 mg buprenorphine hydrochloride (equivalent to 0.3 mg buprenorphine), 50 mg anhydrous dextrose, water for injection, and HCl to adjust pH to 3.5 to 5.5. Buprenorphine hydrochloride has the molecular formula, C29H41NO4·HCl and the molecular weight of 504.09. It has the following structural formula:

CLINICAL PHARMACOLOGY

Buprenorphine hydrochloride is a parenteral opioid analgesic with 0.3 mg buprenorphine being approximately equivalent to 10 mg morphine sulfate in analgesic and respiratory depressant effects in adults. Pharmacological effects occur as soon as 15 minutes after intramuscular injection and persist for 6 hours or longer. Peak pharmacologic effects usually are observed at 1 hour. When used intravenously, the times to onset and peak effect are shortened.

The limits of sensitivity of available analytical methodology precluded demonstration of bioequivalence between intramuscular and intravenous routes of administration. In postoperative adults, pharmacokinetic studies have shown elimination half-lives ranging from 1.2 to 7.2 hours (mean 2.2 hours) after intravenous administration of 0.3 mg of buprenorphine. A single, ten-patient, pharmacokinetic study of doses of 3 mcg/kg in children (age 5 to 7 years) showed a high inter-patient variability, but suggests that the clearance of the drug may be higher in children than in adults. This is supported by at least one repeat-dose study in postoperative pain that showed an optimal inter-dose variable of 4 to 5 hours in pediatric patients as opposed to the recommended 6 to 8 hours in adults.

Buprenorphine, in common with morphine and other phenolic opioid analgesics, is metabolized by the liver and its clearance is related to hepatic blood flow. Studies in patients anesthetized with 0.5% halothane have shown that this anesthetic decreases hepatic blood flow by about 30%.

Mechanism of Analgesic Action: Buprenorphine hydrochloride exerts its analgesic effect via high affinity binding to μ subclass opiate receptors in the central nervous system. Although buprenorphine may be classified as a partial agonist, under the conditions of recommended use it behaves very much like classical μ agonists such as morphine. One unusual property of buprenorphine observed in in vitro studies is its very slow rate of dissociation from its receptor. This could account for its longer duration of action than morphine, the unpredictability of its reversal by opioid antagonists, and its low level of manifest physical dependence.

Narcotic Antagonist Activity: Buprenorphine demonstrates narcotic antagonist activity and has been shown to be equipotent with naloxone as an antagonist of morphine in the mouse tail flick test.

Cardiovascular Effects: Buprenorphine may cause a decrease or, rarely, an increase in pulse rate and blood pressure in some patients.

Effects on Respiration: Under usual conditions of use in adults, both buprenorphine and morphine show similar dose-related respiratory depressant effects. At adult therapeutic doses, buprenorphine hydrochloride (0.3 mg buprenorphine) can decrease respiratory rate in an equivalent manner to an equianalgesic dose of morphine (10 mg). (See WARNINGS.)

INDICATIONS AND USAGE

Buprenorphine hydrochloride injection is indicated for the relief of moderate to severe pain.

CONTRAINDICATION

Buprenorphine hydrochloride should not be administered to patients who have been shown to be hypersensitive to the drug.

WARNINGS

Impaired Respiration: As with other potent opioids, clinically significant respiratory depression may occur within the recommended dose range in patients receiving therapeutic doses of buprenorphine. Buprenorphine hydrochloride should be used with caution in patients with compromised respiratory function (e.g., chronic obstructive pulmonary disease, cor pulmonale, decreased respiratory reserve, hypoxia, hypercapnia, or preexisting respiratory depression). Particular caution is advised if buprenorphine is administered to patients taking or recently receiving drugs with CNS/respiratory depressant effects. In patients with the physical and/or pharmacological risk factors above, the dose should be reduced by approximately one-half.

NALOXONE MAY NOT BE EFFECTIVE IN REVERSING THE RESPIRATORY DEPRESSION PRODUCED BY BUPRENORPHINE. THEREFORE, AS WITH OTHER POTENT OPIOIDS, THE PRIMARY MANAGEMENT OF OVERDOSE SHOULD BE THE RE-ESTABLISHMENT OF ADEQUATE VENTILATION WITH MECHANICAL ASSISTANCE OF RESPIRATION, IF REQUIRED.

Interaction with Other Central Nervous System Depressants: Patients receiving buprenorphine hydrochloride in the presence of other narcotic analgesics, general anesthetics, antihistamines, benzodiazepines, phenothiazines, other tranquilizers, sedative/hypnotics or other CNS depressants (including alcohol) may exhibit increased CNS depression. When such combined therapy is contemplated, it is particularly important that the dose of one or both agents be reduced.

Head Injury and Increased Intracranial Pressure: Buprenorphine hydrochloride, like other potent analgesics, may itself elevate cerebrospinal fluid pressure and should be used with caution in head injury, intracranial lesions and other circumstances where cerebrospinal pressure may be increased. Buprenorphine can produce miosis and changes in the level of consciousness which may interfere with patient evaluation.

Use In Ambulatory Patients: Buprenorphine may impair the mental or physical abilities required for the performance of potentially dangerous tasks such as driving a car or operating machinery. Therefore, buprenorphine hydrochloride should be administered with caution to ambulatory patients who should be warned to avoid such hazards.

Use in Narcotic-Dependent Patients: Because of the narcotic antagonist activity of buprenorphine, use in the physically dependent individual may result in withdrawal effects.

PRECAUTIONS

General:

Buprenorphine hydrochloride should be administered with caution in the elderly, debilitated patients, in children and those with severe impairment of hepatic, pulmonary, or renal function; myxedema or hypothyroidism; adrenal cortical insufficiency (e.g., Addison’s disease); CNS depression or coma; toxic psychoses; prostatic hypertrophy or urethral stricture; acute alcoholism; delirium tremens; or kyphoscoliosis.

Because buprenorphine is metabolized by the liver, the activity of buprenorphine may be increased and/or extended in those individuals with impaired hepatic function or those receiving other agents known to decrease hepatic clearance.

Buprenorphine has been shown to increase intracholedochal pressure to a similar degree as other opioid analgesics, and thus should be administered with caution to patients with dysfunction of the biliary tract.

Information for Patients:

The effects of buprenorphine, particularly drowsiness, may be potentiated by other centrally acting agents such as alcohol or benzodiazepines. It is particularly important that in these circumstances patients must not drive or operate machinery. Buprenorphine has some pharmacologic effects similar to morphine which in susceptible patients may lead to self-administration of the drug when pain no longer exists. Patients must not exceed the dosage of buprenorphine prescribed by their physician. Patients should be urged to consult their physician if other prescription medications are currently being used or are prescribed for future use.

Drug Interactions:

Drug interactions common to other potent opioid analgesics also may occur with buprenorphine. Particular care should be taken when buprenorphine hydrochloride is used in combination with central nervous system depressant drugs (see WARNINGS). Although specific information is not presently available, caution should be exercised when buprenorphine hydrochloride is used in combination with MAO inhibitors. There have been reports of respiratory and cardiovascular collapse in patients who received therapeutic doses of diazepam and buprenorphine. A suspected interaction between buprenorphine hydrochloride and phenprocoumon resulting in purpura has been reported.

CYP3A4 Inhibitors:

Since the metabolism of buprenorphine is mediated by the CYP3A4 isozyme, coadministration of drugs that inhibit CYP3A4 activity may cause decreased clearance of buprenorphine. Thus patients coadministered with inhibitors of CYP3A4 such as macrolide antibiotics (e.g., erythromycin), azole antifungal agents (e.g., ketoconazole), and protease inhibitors (e.g., ritanovir) while receiving buprenorphine should be carefully monitored and dosage adjustment made if warranted.

CYP3A4 Inducers:

Cytochrome P450 inducers, such as rifampin, carbamazepine, and phenytoin, induce metabolism and as such may cause increased clearance of buprenorphine. Caution is advised when administering buprenorphine to patients receiving these medications and if necessary dose adjustments should be considered.

Carcinogenesis, Mutagenesis and Impairment of Fertility:

Carcinogenesis: Carcinogenicity studies were conducted in Sprague-Dawley rats and CD-1 mice. Buprenorphine was administered in the diet at doses of 0.6, 5.5 and 56 mg/kg/day for 27 months in rats. These doses were approximately equivalent to 5.7, 52 and 534 times the recommended human dose (1.2 mg) on a mg/m^2 body surface area basis. Statistically significant dose-related increases in testicular interstitial (Leydig’s) cell tumors occurred, according to the trend test adjusted for survival. Pairwise comparison of the high dose against control failed to show statistical significance. In the mouse study, buprenorphine was administered in the diet at doses of 8, 50, and 100 mg/kg/day for 86 weeks.

The high dose was approximately equivalent to 477 times the recommended human dose (1.2 mg) on a mg/m^2 basis. Buprenorphine was not carcinogenic in mice.

Mutagenesis: Buprenorphine was studied in a series of tests. Results were negative in Chinese hamster bone marrow and spermatogonia cells, and negative in mouse lymphoma L5178Y assay. Results were equivocal in the Ames test: negative in studies in two laboratories, but positive in frame shift mutation at high dose (5 mg/plate) in a third study.

Impairment of Fertility: Reproduction studies of buprenorphine in rats demonstrated no evidence of impaired fertility at daily oral doses up to 80 mg/kg (approximately 763 times the recommended human daily dose of 1.2 mg on a mg/m^2 basis) or up to 5 mg/kg I.M. or S.C. (approximately 48 times the recommended human daily dose of 1.2 mg on a mg/m^2 basis).

Pregnancy: Pregnancy Category C.

Teratogenic effects: Buprenorphine was not teratogenic in rats or rabbits after I.M. or S.C. doses up to 5 mg/kg/day (approximately 48 and 95 times the recommended human daily dose of 1.2 mg on a mg/m^2 basis), I.V. doses up to 0.8 mg/kg/day (approximately 8 times and 15 times the recommended human daily dose of 1.2 mg on a mg/m^2 basis), or oral doses up to 160 mg/kg/day in rats (approximately 1525 times the recommended human daily dose of 1.2 mg on a mg/m^2 basis) and 25 mg/kg/day in rabbits (approximately 475 times the recommended human daily dose of 1.2 mg on a mg/m^2 basis). Significant increases in skeletal abnormalities (e.g. extra thoracic vertebra or thoraco-lumbar ribs) were noted in rats after S.C. administration of 1 mg/kg/day and up (approximately 9.5 times the recommended human daily dose of 1.2 mg on a mg/m^2 basis) and in rabbits after I.M. administration of 5 mg/kg/day (approximately 95 times the recommended human daily dose of 1.2 mg on a mg/m^2 basis), but these increases were not statistically significant. Increases in skeletal abnormalities after oral administration were not observed in rats, and increases in rabbits (1-25 mg/kg/day) were not statistically significant.

There are no adequate and well-controlled studies in pregnant women. Buprenorphine hydrochloride should be used during pregnancy only if the potential benefit justifies the potential risk to the fetus.

Labor and Delivery:

The safety of buprenorphine given during labor and delivery has not been established.

Nursing Mothers:

An apparent lack of milk production during general reproduction studies with buprenorphine in rats caused decreased viability and lactation indices. Use of high doses of sublingual buprenorphine in pregnant women showed that buprenorphine passes into the mother’s milk. Breast-feeding is therefore not advised in nursing mothers treated with buprenorphine.

Pediatric Use:

The safety and effectiveness of buprenorphine have been established for children between 2 and 12 years of age. Use of buprenorphine in children is supported by evidence from adequate and well controlled trials of buprenorphine in adults, with additional data from studies of 960 children ranging in age from 9 months to 18 years of age. Data is available from a pharmaco-kinetic study, several controlled clinical trials, and several large post-marketing studies and case series. The available information provides reasonable evidence that buprenorphine may be used safely in children ranging from 2 to 12 years of age, and that it is of similar effectiveness in children as in adults.

ADVERSE REACTIONS

The most frequent side effect in clinical studies involving 1,133 patients was sedation which occurred in approximately two-thirds of the patients. Although sedated, these patients could easily be aroused to an alert state.

Other less frequent adverse reactions occurring in 5 to 10% of the patients were:

 | Nausea | Dizziness/Vertigo

Occurring in 1 to 5% of the patients:

 | Sweating | Headache
 | Hypotension | Nausea/Vomiting
 | Vomiting | Hypoventilation
 | Miosis

The following adverse reactions were reported to have occurred in less than 1% of the patients:

CNS Effect: confusion, blurred vision, euphoria, weakness/fatigue, dry mouth, nervousness, depression, slurred speech, paresthesia.

Cardiovascular: hypertension, tachycardia, bradycardia.

Gastrointestinal: constipation.

Respiratory: dyspnea, cyanosis.

Dermatological: pruritus.

Ophthalmological: diplopia, visual abnormalities.

Miscellaneous: Injection site reaction, urinary retention, dreaming, flushing/warmth, chills/cold, tinnitus, conjunctivitis, Wenckebach block, and psychosis.

Other effects observed infrequently include malaise, hallucinations, depersonalization, coma, dyspepsia, flatulence, apnea, rash, amblyopia, tremor, and pallor.

The following reactions have been reported to occur rarely: loss of appetite, dysphoria/agitation, diarrhea, urticaria, and convulsions/lack of muscle coordination.

Allergic Reactions: Cases of acute and chronic hypersensitivity to buprenorphine have been reported both in clinical trials and in the postmarketing experience of buprenorphine and other buprenorphine-containing products. The most common signs and symptoms include rashes, hives, and pruritus. Cases of bronchospasm, angioneurotic edema, and anaphylactic shock have been reported. A history of hypersensitivity to buprenorphine is a contraindication to buprenorphine.

In the United Kingdom, buprenorphine hydrochloride was made available under monitored release regulation during the first year of sale, and yielded data from 1,736 physicians on 9,123 patients (17,120 administrations). Data on 240 children under the age of 18 years were included in this monitored release program. No important new adverse effects attributable to buprenorphine hydrochloride were observed.

DRUG ABUSE AND DEPENDENCE

Buprenorphine hydrochloride is a partial agonist of the morphine type: i.e., it has certain opioid properties which may lead to psychic dependence of the morphine type due to an opiate-like euphoric component of the drug. Direct dependence studies have shown little physical dependence upon withdrawal of the drug. However, caution should be used in prescribing to individuals who are known to be drug abusers or ex-narcotic addicts. The drug may not substitute in acutely dependent narcotic addicts due to its antagonist component and may induce withdrawal symptoms.

OVERDOSAGE

Manifestations: Clinical experience with buprenorphine overdosage has been insufficient to define the signs of this condition at this time. Although the antagonist activity of buprenorphine may become manifest at doses somewhat above the recommended therapeutic range, doses in the recommended therapeutic range may produce clinically significant respiratory depression in certain circumstances. (See WARNINGS.)

Treatment: The respiratory and cardiac status of the patients should be monitored carefully. Primary attention should be given to the re-establishment of adequate respiratory exchange through provision of a patent airway and institution of assisted or controlled ventilation. Oxygen, intravenous fluids, vasopressors, and other supportive measures should be employed as indicated. Doxapram, a respiratory stimulant, may be used. NALOXONE MAY NOT BE EFFECTIVE IN REVERSING THE RESPIRATORY DEPRESSION PRODUCED BY BUPRENORPHINE. THEREFORE, AS WITH OTHER POTENT OPIOIDS, THE PRIMARY MANAGEMENT OF OVERDOSE SHOULD BE THE RE-ESTABLISHMENT OF ADEQUATE VENTILATION WITH MECHANICAL ASSISTANCE OF RESPIRATION, IF REQUIRED.

DOSAGE AND ADMINISTRATION

Adults: The usual dosage for persons 13 years of age and over is 1 mL buprenorphine hydrochloride injection (0.3 mg buprenorphine) given by deep intramuscular or slow (over at least 2 minutes) intravenous injection at up to 6-hour intervals, as needed. Repeat once (up to 0.3 mg) if required, 30 to 60 minutes after initial dosage, giving consideration to previous dose pharmacokinetics, and thereafter only as needed. In high-risk patients (e.g., elderly, debilitated, presence of respiratory disease, etc.) and/or in patients where other CNS depressants are present, such as in the immediate postoperative period, the dose should be reduced by approximately one-half. Extra caution should be exercised with the intravenous route of administration, particularly with the initial dose.

Occasionally, it may be necessary to administer single doses of up to 0.6 mg to adults depending on the severity of the pain and the response of the patient. This dose should only be given IM and only to adult patients who are not in a high risk category (see WARNINGS and PRECAUTIONS). At this time, there are insufficient data to recommend single doses greater than 0.6 mg for long-term use.

Children: Buprenorphine hydrochloride has been used in children 2 to 12 years of age at doses between 2 to 6 micrograms/kg of body weight given every 4 to 6 hours. There is insufficient experience to recommend a dose in infants below the age of two years, single doses greater than 6 micrograms/kg of body weight, or the use of a repeat or second dose at 30 to 60 minutes (such as is used in adults). Since there is some evidence that not all children clear buprenorphine faster than adults, fixed interval or "round-the-clock" dosing should not be undertaken until the proper inter-dose interval has been established by clinical observation of the child. Physicians should recognize that, as with adults, some pediatric patients may not need to be remedicated for 6 to 8 hours.

Safety and Handling: Buprenorphine hydrochloride injection is supplied in sealed cartridges and poses no known environmental risk to health care providers. Accidental dermal exposure should be treated by removal of any contaminated clothing and rinsing the affected area with water.

Buprenorphine is a potent narcotic, and like all drugs of this class has been associated with abuse and dependence among health care providers. To control the risk of diversion, it is recommended that measures appropriate to the health care setting be taken to provide rigid accounting, control of wastage, and restriction of access.

Parenteral drug products should be inspected visually for particulate matter and discoloration prior to administration, whenever solution and container permit.

HOW SUPPLIED

List | Container | Concentration | Fill | Quantity
2012 | Carpuject® | 0.3 mg base/mL | 1 mL | 10
 | (22-Gauge, 1¼" Needle)
2012 | Carpuject® | 0.3 mg base/mL | 1 mL | 10
 | with Luer Lock

Store at 20° to 25°C (68° to 77°F) [see USP Controlled Room Temperature.]

Protect from prolonged exposure to light.

Retain in carton until time of use.

Do not freeze.

Revised: June, 2009

Printed in USA |  | EN-2088

Hospira, Inc., Lake Forest, IL 60045, USA

Repackaged by: Rebel Distributors Corp, Thousand Oaks, CA 91320